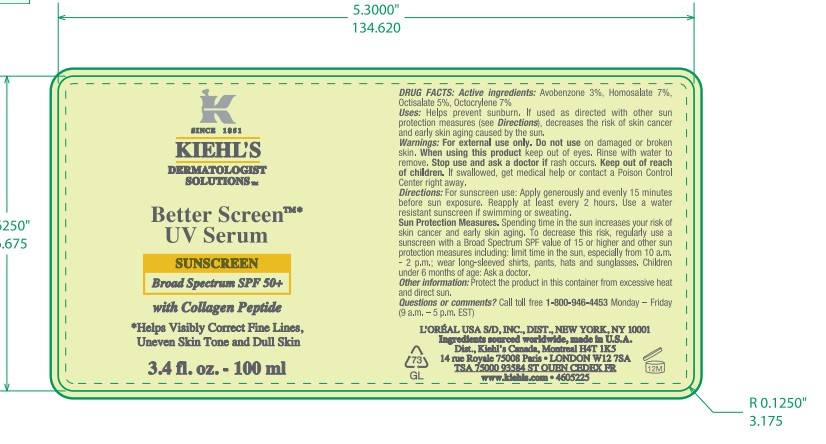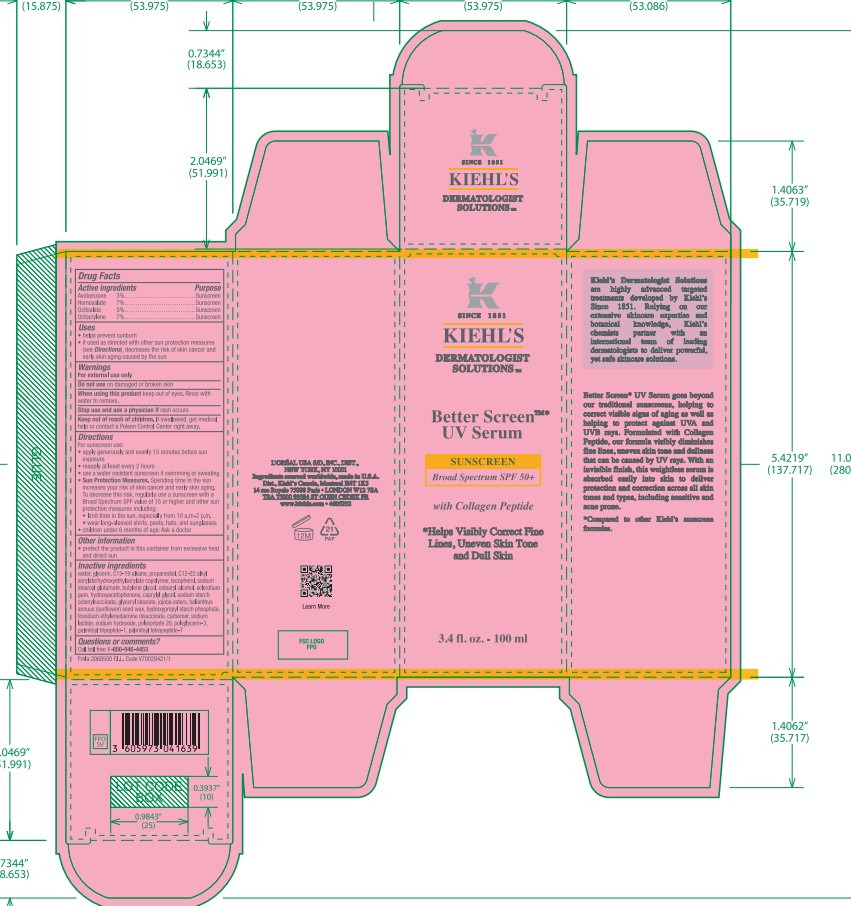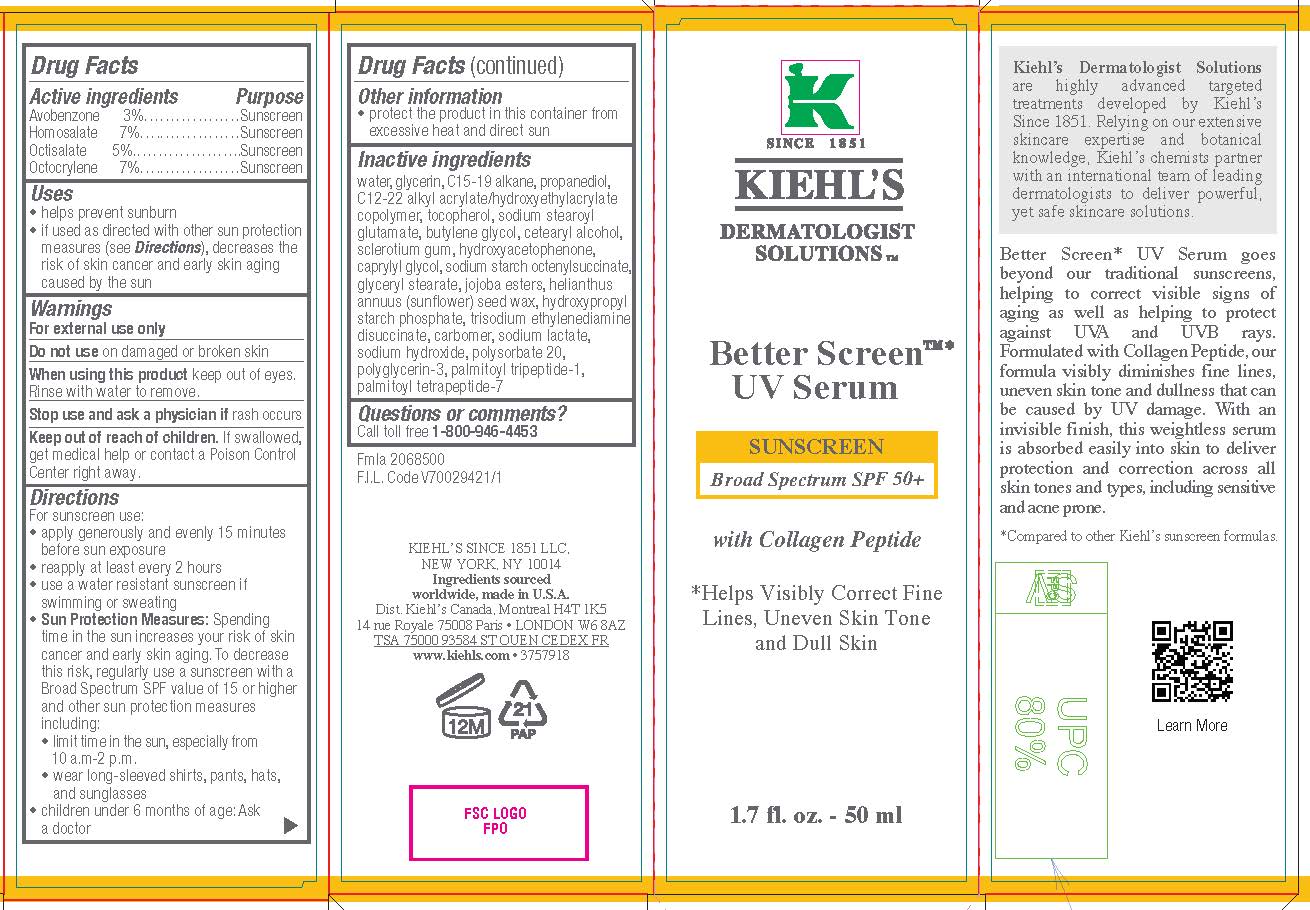 DRUG LABEL: Kiehls Dermatologist Solutions Better Screen UV Serum Broad Spectrum SPF 50 Plus Sunscreen
NDC: 49967-053 | Form: LOTION
Manufacturer: L'Oreal USA Products Inc
Category: otc | Type: HUMAN OTC DRUG LABEL
Date: 20250711

ACTIVE INGREDIENTS: AVOBENZONE 30 mg/1 mL; HOMOSALATE 70 mg/1 mL; OCTISALATE 50 mg/1 mL; OCTOCRYLENE 70 mg/1 mL
INACTIVE INGREDIENTS: WATER; GLYCERIN; C15-19 ALKANE; PROPANEDIOL; TOCOPHEROL; SODIUM STEAROYL GLUTAMATE; BUTYLENE GLYCOL; CETOSTEARYL ALCOHOL; BETASIZOFIRAN; HYDROXYACETOPHENONE; CAPRYLYL GLYCOL; GLYCERYL MONOSTEARATE; HYDROGENATED JOJOBA OIL/JOJOBA OIL, RANDOMIZED (IODINE VALUE 64-70); HELIANTHUS ANNUUS SEED WAX; TRISODIUM ETHYLENEDIAMINE DISUCCINATE; CARBOMER HOMOPOLYMER, UNSPECIFIED TYPE; SODIUM LACTATE; SODIUM HYDROXIDE; POLYSORBATE 20; POLYGLYCERIN-3; PALMITOYL TRIPEPTIDE-1; PALMITOYL TETRAPEPTIDE-7

Drug Facts

Active ingredients

Avobenzone 3%

Homosalate 7%

Octisalate 5%

Octocrylene 7%

Purpose

Sunscreen

Uses

- helps prevent sunburn
- if used as directed with other sun protection measures (see Directions), decreases the risk of skin cancer and early skin aging caused by the sun

Warnings

For external use only

Flammble until dry. Do not use near fire, flame or heat.

Do not use

on damaged or broken skin

When using this product

keep out of eyes. Rinse with water to remove.

Stop use and ask a doctor if

rash occurs

Keep out of reach of children.

If swallowed, get medical help or contact a Poison Control Center right away.

Directions

- shake well before use
- apply liberally 15 minutes before sun exposure
- reapply at least every 2 hours
- use a water resistant sunscreen if swimming or sweating
- Sun Protection Measures. Spending time in the sun increases your risk of skin cancer and early skin aging. To decrease this risk, regularly use a sunscreen with a Broad Spectrum SPF value of 15 or higher and other sun protection measures including:
- limit time in the sun, especially from 10 a.m. - 2p.m.
- wear long-sleeved shirts, pants, hats and sunglasses
- children under 6 months of age: Ask a doctor

Other information

- protect the product in this container from excessive heat and direct sun

Inactive ingredients

water, glycerin, c15-19 alkane, propanediol, c12-22 alkyl acrylate/hydroxyethylacrylate copolymer, tocopherol, sodium stearoyl glutamate, butylene glycol, cetearyl alcohol, sclerotium gum, hydroxyacetophenone, caprylyl glycol, sodium starch octenylsuccinate, glyceryl stearate, jojoba esters, helianthus annuus (sunflower) seed wax, hydroxypropyl starch phosphate, trisodium ethylenediamine disuccinate, carbomer, sodium lactate, sodium hydroxide, polysorbate 20, polyglycerin-3, palmitoyl tripeptide-1, palmitoyl tetrapeptide-7